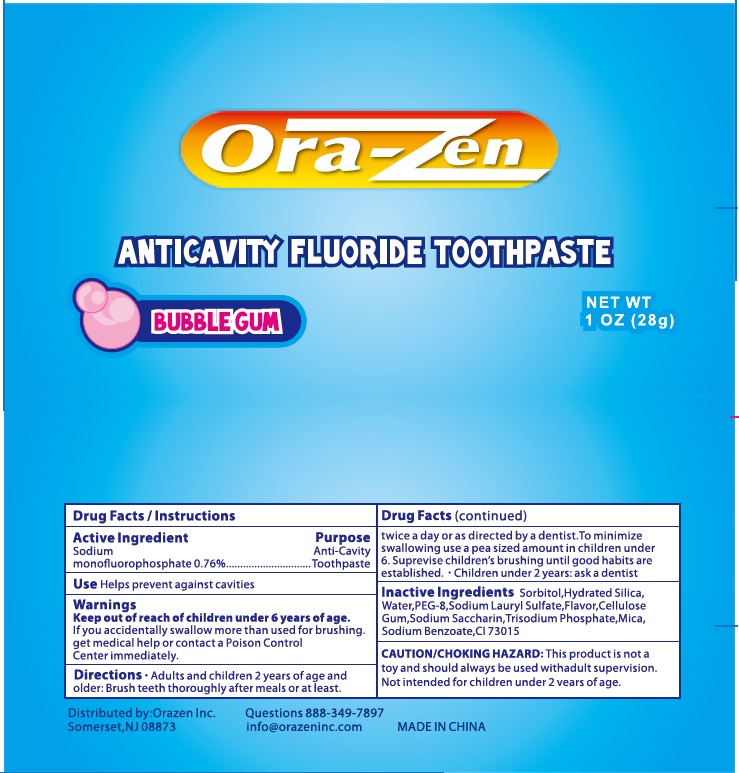 DRUG LABEL: Orazen
NDC: 71927-102 | Form: PASTE
Manufacturer: Orazen Inc
Category: otc | Type: HUMAN OTC DRUG LABEL
Date: 20230813

ACTIVE INGREDIENTS: SODIUM MONOFLUOROPHOSPHATE 0.1 g/100 g
INACTIVE INGREDIENTS: SORBITOL; HYDRATED SILICA; WATER; POLYETHYLENE GLYCOL 400; CARBOXYMETHYLCELLULOSE SODIUM; SODIUM LAURYL SULFATE; MICA; SODIUM BENZOATE; TRISODIUM PHOSPHIDE; FD&C BLUE NO. 2; POTASSIUM SODIUM SACCHARATE

Orazen Kids Anticavity Toothpaste

Active Ingredient

Sodium Monofluorophosphate 0.76%

Purpose
Anti-Cavity Toothpaste

INDICATIONS AND USAGE

Use: Helps prevent against cavities

Keep out of reach of children under 6 years of age.

WARNINGS

Warnings: If you accidentally swallow more than used for brushing,get medical help or contact a Poison Control Center immediately.

DOSAGE AND ADMINISTRATION

Directions:adults and children 2yrs.and older: brush teeth thoroughly after meals or at least twice a day or use as directed by a dentist. To minimize swallowing use a pea sized amount in children under 6. Supervise children's brushing until good habits are established. Children under 2 yrs.:ask a dentist

INACTIVE INGREDIENT

Inactive Ingredients: Sorbitol, Hydrated Silica, Water, Peg-8, Sodium Lauryl Sulfate, Flavor, Cellulose Gum, Sodium Saccharin, Trisodium Phospate, Mica, Sodium Benzoate, CI 73015

DESCRIPTION

Orazen

Orazen Inc

Somerset, NJ 08873

Questions 888-349-7897

Info@orazeninc.com

Made in China/Hecho en China

Fabrique en Chine

PACKAGE LABEL

Ora-Zen Anticavity Toothpaste

Bubblegum